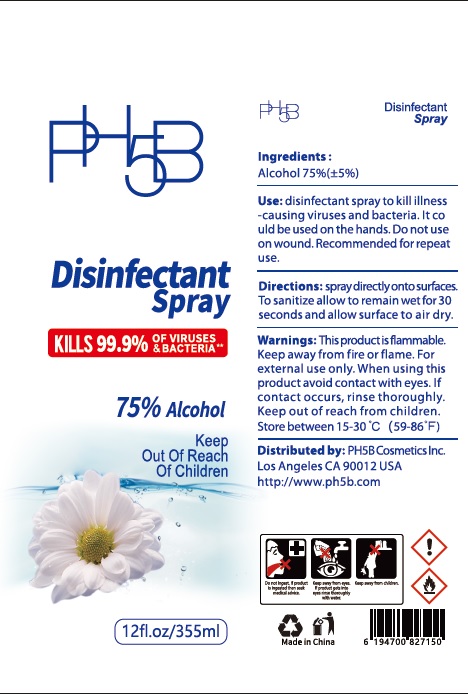 DRUG LABEL: PH5B Disinfectant
NDC: 76718-016 | Form: SPRAY
Manufacturer: Guangzhou Jukang Sanitary Products Co., Ltd.
Category: otc | Type: HUMAN OTC DRUG LABEL
Date: 20201020

ACTIVE INGREDIENTS: ALCOHOL 75 mL/100 mL
INACTIVE INGREDIENTS: WATER; GLYCERIN

Active ingredient

Alcohol 75% (±5%)

Purpose

Anti-bacteria

INDICATIONS AND USAGE

disinfectant spray to kill illness-causing viruses ad bacteria. It can be used on household srufaces including the kitchen, bathroom, and other high-activity areas.

KEEP OUT OF REACH OF CHILDREN

supervise children under 6 years of age when using this product to avoid swallowing. If swallowed get medical.

warnings:

For external use only.

Flabbable, keep away from fire or flame.

When using this product, avoid contact with eyes, If contact occurs, rinse thoroughly.

Stop use and ask a doctor if irritation and rash occurs.

Avoid freezing and excessive heat above 40℃ (104℉)

Store beween 15-30 ℃ （59-86℉）

DOSAGE AND ADMINISTRATION

spray directly onto surface. To sanitize allow to remain wet for 30 seconds and allow surface to air dry.

Inactive ingredients

glycerin, water